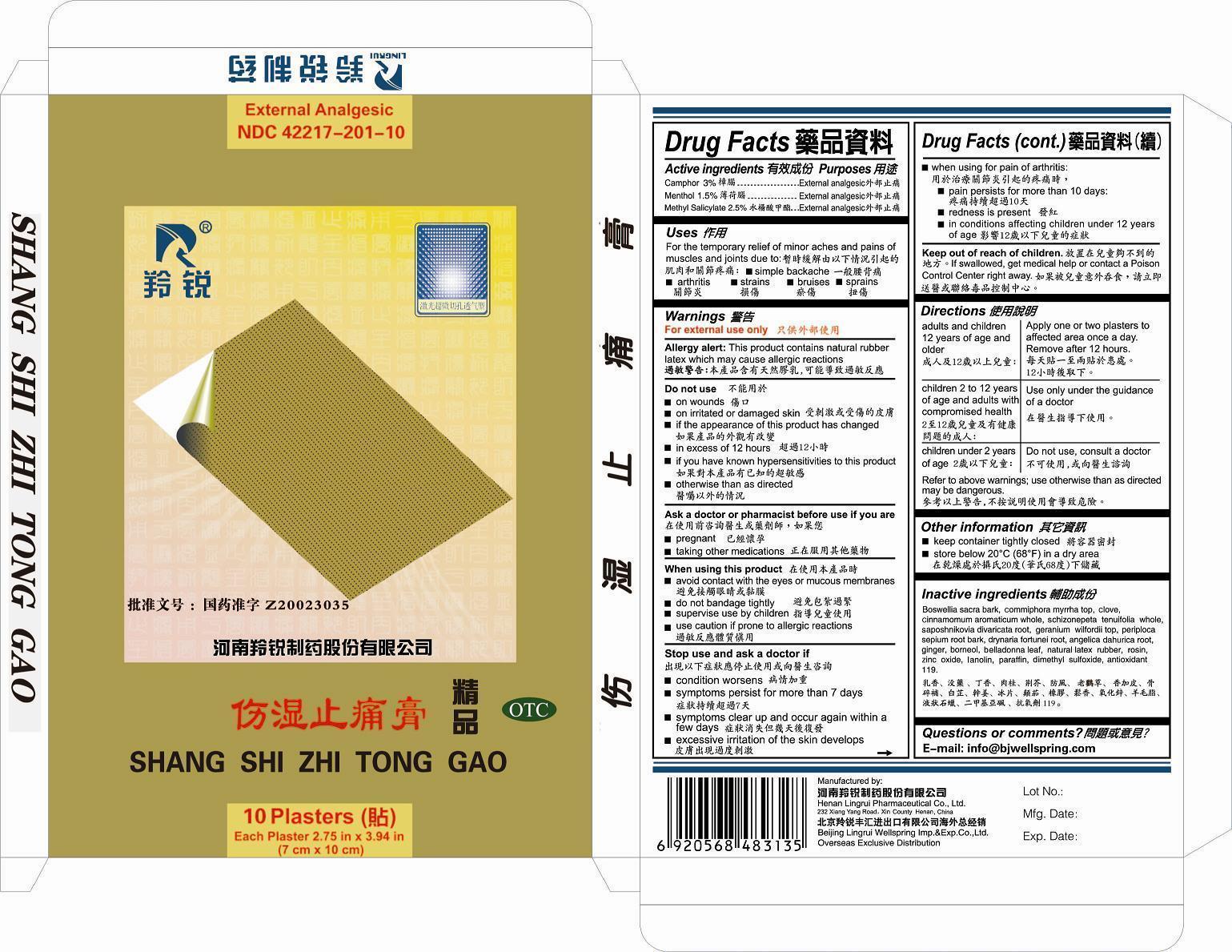 DRUG LABEL: Shang Shi Zhi Tong Gao
NDC: 42217-201 | Form: PLASTER
Manufacturer: Henan Lingrui Pharmaceutical Co.; Ltd
Category: otc | Type: HUMAN OTC DRUG LABEL
Date: 20140227

ACTIVE INGREDIENTS: CAMPHOR (NATURAL) 3.0 g/100 g; MENTHOL 1.5 g/100 g; METHYL SALICYLATE 2.5 g/100 g
INACTIVE INGREDIENTS: BOSWELLIA SACRA BARK; COMMIPHORA MYRRHA TOP; CLOVE; CINNAMOMUM AROMATICUM WHOLE; SCHIZONEPETA TENUIFOLIA WHOLE; SAPOSHNIKOVIA DIVARICATA ROOT; GERANIUM WILFORDII TOP; PERIPLOCA SEPIUM ROOT BARK; DRYNARIA FORTUNEI ROOT; ANGELICA DAHURICA ROOT; GINGER; BORNEOL; BELLADONNA LEAF; NATURAL LATEX RUBBER; ROSIN; ZINC OXIDE; LANOLIN; PARAFFIN; DIMETHYL SULFOXIDE; ANTIOXIDANT 119

Henan Lingrui Pharmaceutical Co.; Ltd

ACTIVE INGREDIENTS

Camphor 3.0%

Menthol 1.5%

Methyl Salicylate 2.5%

PURPOSE

Camphor External Analgesic

Menthol External Analgesic

Methyl Salicylate External Analgesic

USES

To relieve the rheumatic pain and arthralgia by promoting blood circulation, used for rheumatoid arthristis muscular aches, sprain etc.

WARNINGS

For external use only.

Agergy Alert: This product contains natural rubber latex which may cause allergic reactions.

DO NOT USE

on wounds.

on irritated or damaged skin

if the apperance of this product has changed

in excess of 12 hours

if you have know hypersensitivities to this product

otherwise than as directed

Ask a Doctor or Pharmacist before use if you are

Pregnent

taking other medications

When using this product

avoid contact iwth the eyes or mucous membrances

do not bandage tightly

supervise use by children

use caution if prone to allergic reactions

Stop use and ask a doctor if

condition worsens

symptonms persist for more than 7 days

symptoms clear up and occur again within 1 few days

excessive irritation of the skin develops

when using for pain of arthritis

pain persists for more than 10 days

redness is present

in conditions affecting children under 12 years

Keep out of reach of children. If swallowed, get medical help or Poison Control Center right away.

Adults and children 12 years of age and older: Apply one or two plasters to affected area once a day. Remove after 12 hours. DIRECTIONB Refer to the above warnings: use otherwise than as directed may be dangerous.

Adults and children 12 years of age and older: Apply one or two plasters to affected area once a day. Remove after 12 hours.
Children 2 to 12 years of age and adults with compromised health: Use only under the guidance of a doctor.
Children under 2 years of age: Do not use, consult a doctor.
Refer to the above warnings: use otherwise than as directed may be dangerous.

OTHER INFORMATION

Keep container tightly closed.

Store below 20 degree centigrade (68 E F) in a dry area.

INACTIVE INGREDIENTS

BOSWELLIA SACRA BARK, COMMIPHORA MYRRHA TOP, CLOVE, CINNAMOMUM AROMATICUM WHOLE, SCHIZONEPETA TENUIFOLIA WHOLE, SAPOSHNIKOVIA DIVARICATA ROOT, GERANIUM WILFORDII TOP, PERIPLOCA SEPIUM ROOT BARK, DRYNARIA FORTUNEI ROOT, ANGELICA DAHURICA ROOT, GINGER, BORNEOL, BELLADONNA LEAF, NATURAL LATEX RUBBER, ROSIN, ZINC OXIDE, LANOLIN, PARAFFIN, DIMETHYL SULFOXIDE, ANTIOXIDANT 119

Questions or Commnets?

E-mail: info@bjwellspring.com